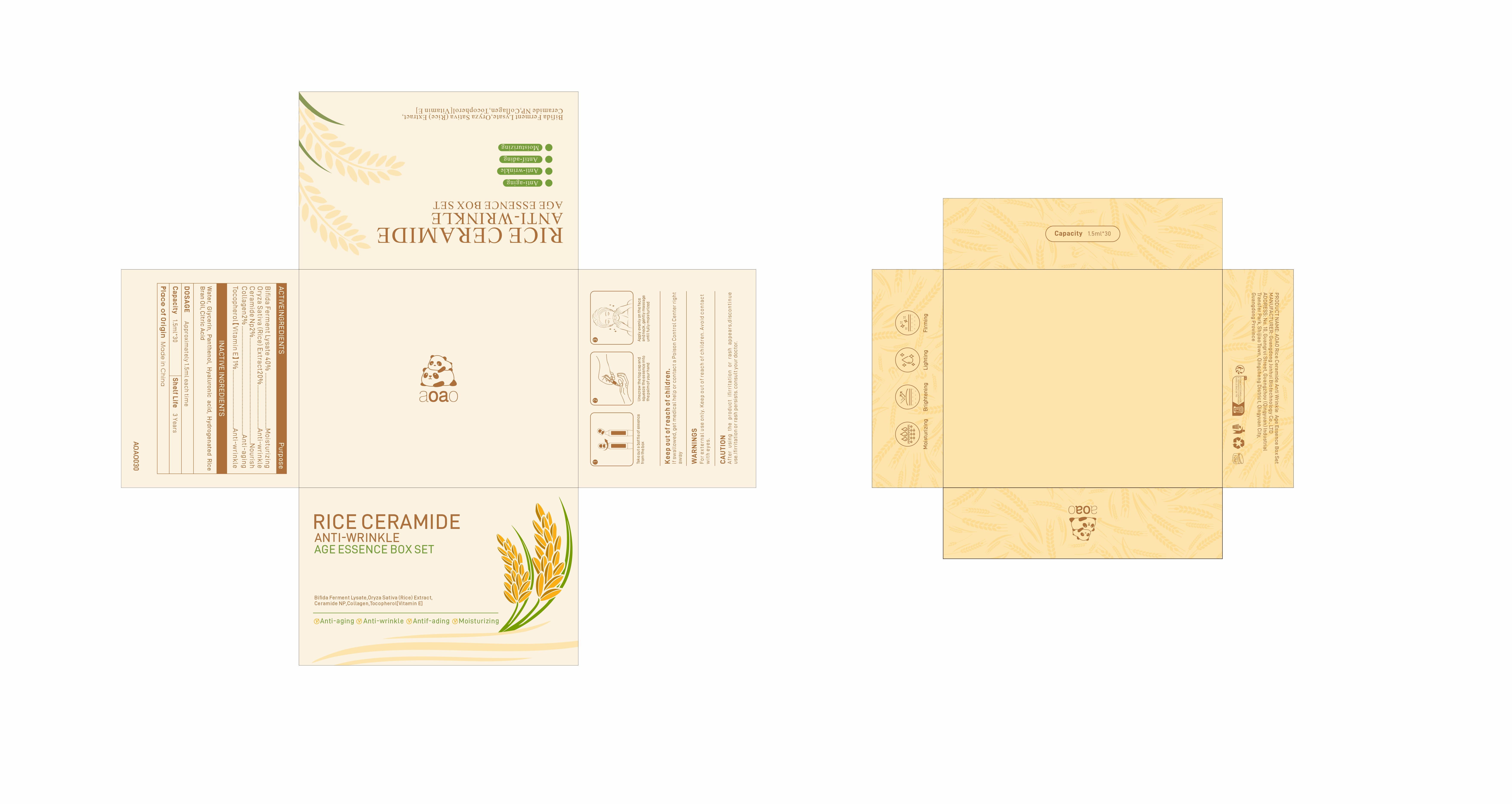 DRUG LABEL: A0A0 Rice Ceramide Anti Wrinkle Age Essence Box Set
NDC: 84509-015 | Form: CREAM
Manufacturer: Guangdong Junhui Biotechnology Co., LTD
Category: otc | Type: HUMAN OTC DRUG LABEL
Date: 20250108

ACTIVE INGREDIENTS: RICE GERM 300 mg/1.5 mL; CERAMIDE NP 30 mg/1.5 mL; COLLAGEN, SOLUBLE, FISH SKIN 30 mg/1.5 mL; FERMENT COMPLEX 6/PF 600 mg/1.5 mL; TOCOPHEROL 15 mg/1.5 mL
INACTIVE INGREDIENTS: RICE BRAN OIL; GLYCERIN; PANTHENOL; HYALURONIC ACID; CITRIC ACID MONOHYDRATE; WATER

Active Ingredients

Bifida Ferment Lysate 40%
Oryza Sativa (Rice) Extract 20%
Ceramide NP 2%
Collagen 2%
Tocopherol 1%

Purpose

Moisturizing
Anti-wrinkle
Nourish
Anti-aging

Uses

①Take out a bottle of essence from the box
②Unscrew the top cap and squeeze the essence intothe palm of your hand

③Apply evenly on the face and neck,gently massage until fully moisturized

Warnings

For external use only. Keep out ofreach of children.Avoid contact with eyes.

CAUTION

After using the product ifirritation or rash appears,discontinue use.Ifirritation or
rash persists.consult your doctor.

Product Name

A0A0 Rice Ceramide Anti Wrinkle Age Essence Box Set

DOSAGE

Approximately 1.5ml each time

Inactive Ingredients

Water,Glycerin，Panthenol,Hyaluronic acid,Hydrogenated Rice Bran Oil，Citric Acid

Manufacturer

Guangdong Junhui Biotechnology Co., LTD

Capacity

1.5ml*30

Shelf Life

3 Years

Place of Origin

Made in China